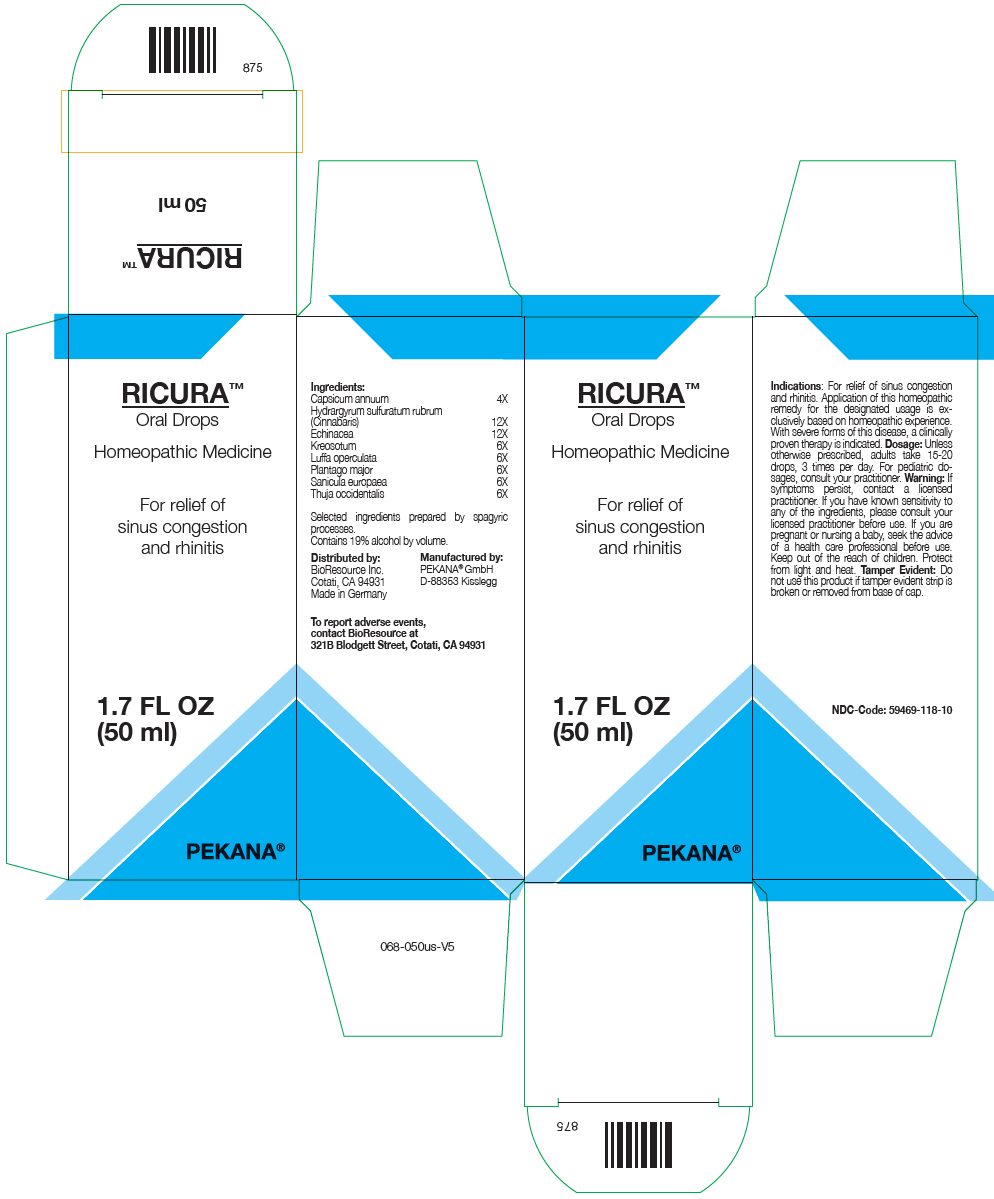 DRUG LABEL: RICURA
NDC: 59469-118 | Form: SOLUTION/ DROPS
Manufacturer: PEKANA Naturheilmittel GmbH
Category: homeopathic | Type: HUMAN OTC DRUG LABEL
Date: 20221219

ACTIVE INGREDIENTS: Paprika 4 [hp_X]/50 mL; Mercuric Sulfide 12 [hp_X]/50 mL; Wood Creosote 6 [hp_X]/50 mL; Luffa Operculata Fruit 6 [hp_X]/50 mL; Thuja Occidentalis Leafy Twig 6 [hp_X]/50 mL; Echinacea, Unspecified 12 [hp_X]/50 mL; Plantago Major Leaf 6 [hp_X]/50 mL; Sanicula Europaea Top 6 [hp_X]/50 mL
INACTIVE INGREDIENTS: Water; Alcohol

RICURA™

ACTIVE INGREDIENT

Ingredients:
Capsicum annuum | 4X
Hydrargyrum sulfuratum rubrum (Cinnabaris) | 12X
Echinacea | 12X
Kreosotum | 6X
Luffa operculata | 6X
Plantago major | 6X
Sanicula europaea | 6X
Thuja occidentalis | 6X

Selected ingredients prepared by spagyric processes.

INACTIVE INGREDIENT

Contains 19% alcohol by volume.

Indications

PURPOSE

For relief of sinus congestion and rhinitis. Application of this homeopathic remedy for the designated usage is exclusively based on homeopathic experience. With severe forms of this disease, a clinically proven therapy is indicated.

Dosage

Unless otherwise prescribed, adults take 15-20 drops, 3 times per day. For pediatric dosages, consult your practitioner.

Warning

ASK DOCTOR

If symptoms persist, contact a licensed practitioner. If you have known sensitivity to any of the ingredients, please consult your licensed practitioner before use. If you are pregnant or nursing a baby, seek the advice of a health care professional before use.

Keep out of the reach of children.

STORAGE AND HANDLING

Protect from light and heat.

Tamper Evident

Do not use this product if tamper evident strip is broken or removed from base of cap.

QUESTIONS

To report adverse events, contact BioResource at 321B Blodgett Street, Cotati, CA 94931

Distributed by:
BioResource Inc.
Cotati, CA 94931

Manufactured by:
PEKANA® GmbH
D-88353 Kisslegg

PRINCIPAL DISPLAY PANEL - 50 ml Bottle Box

RICURA™
Oral Drops

Homeopathic Medicine

For relief of
sinus congestion
and rhinitis

1.7 FL OZ
(50 ml)

PEKANA®